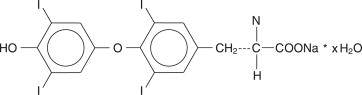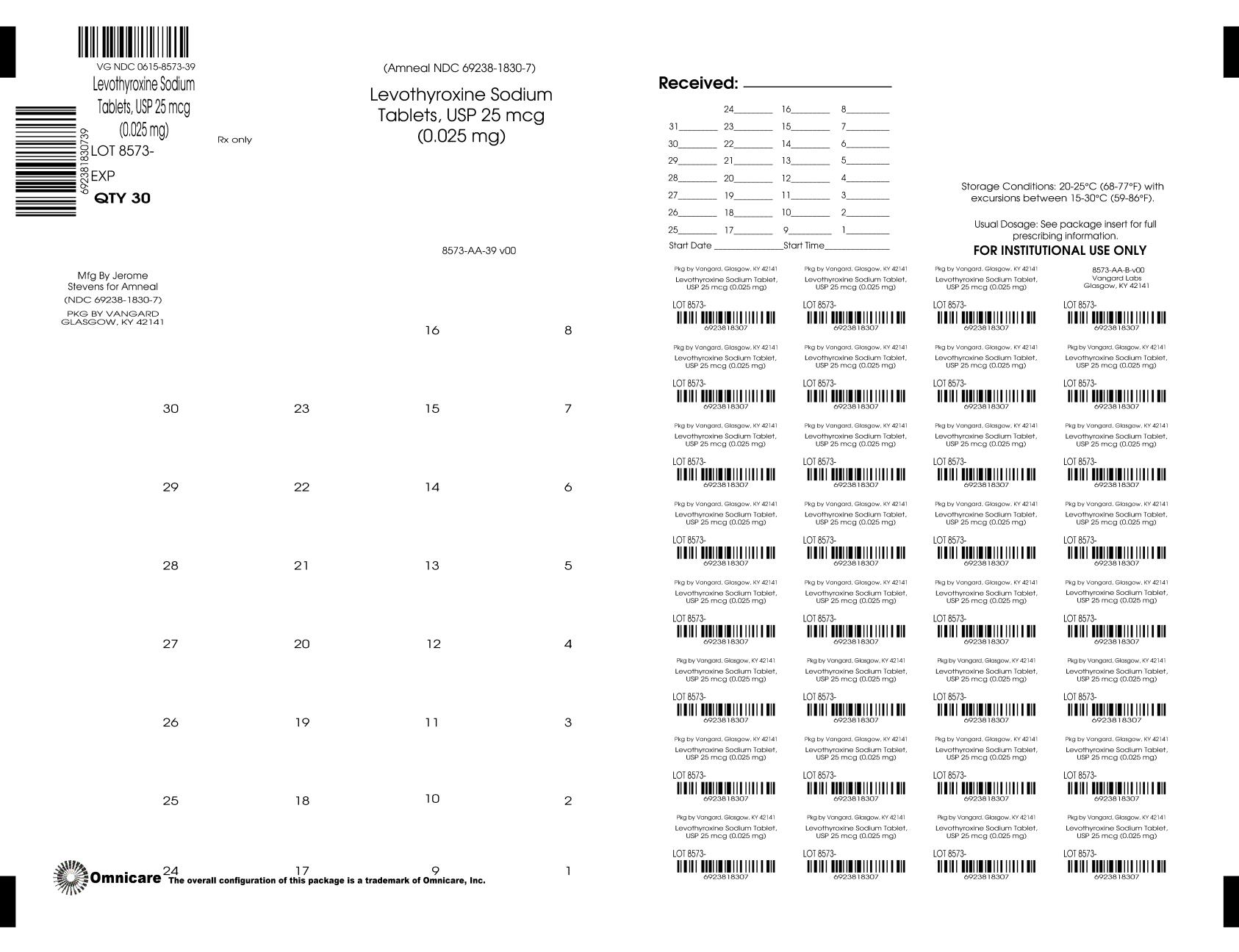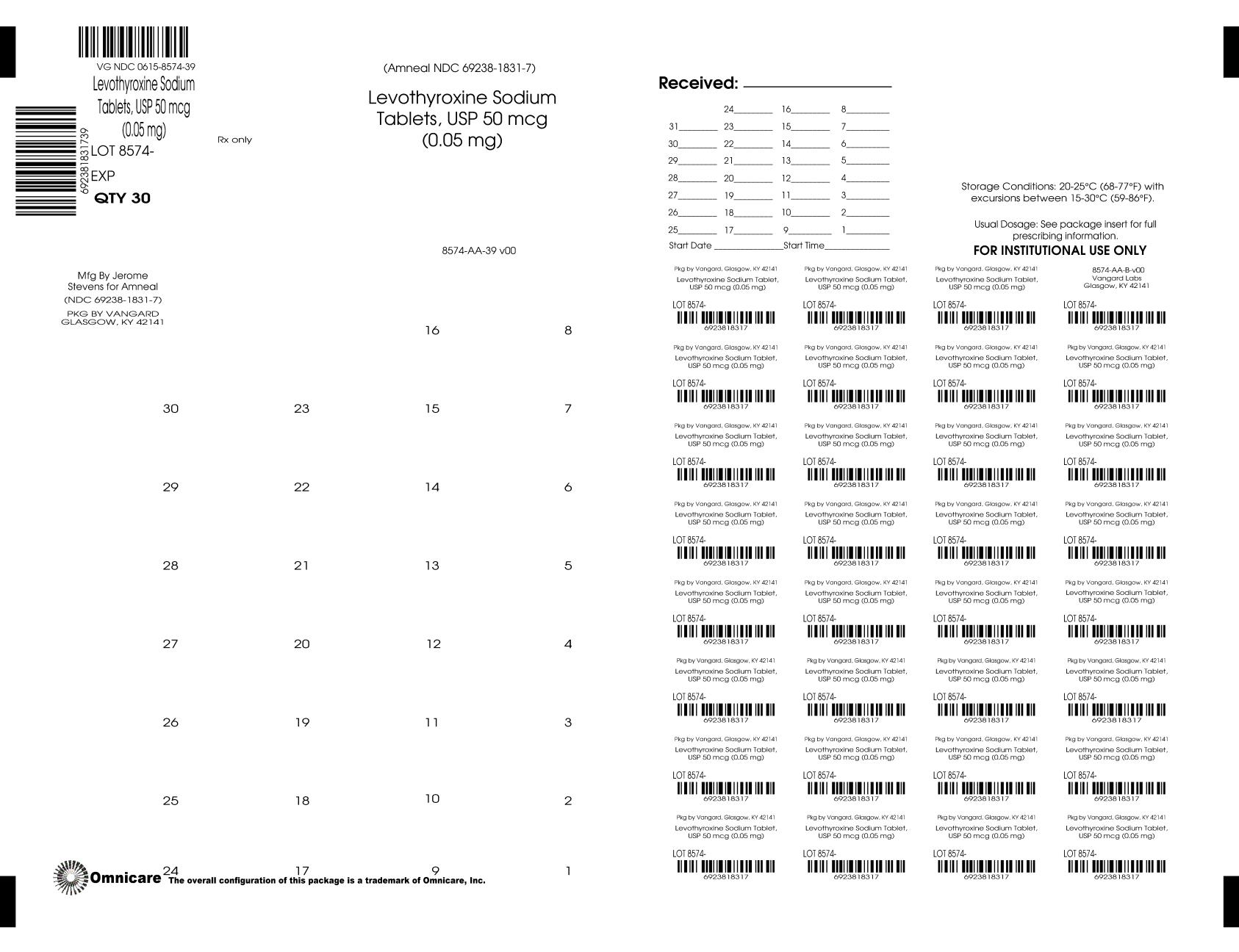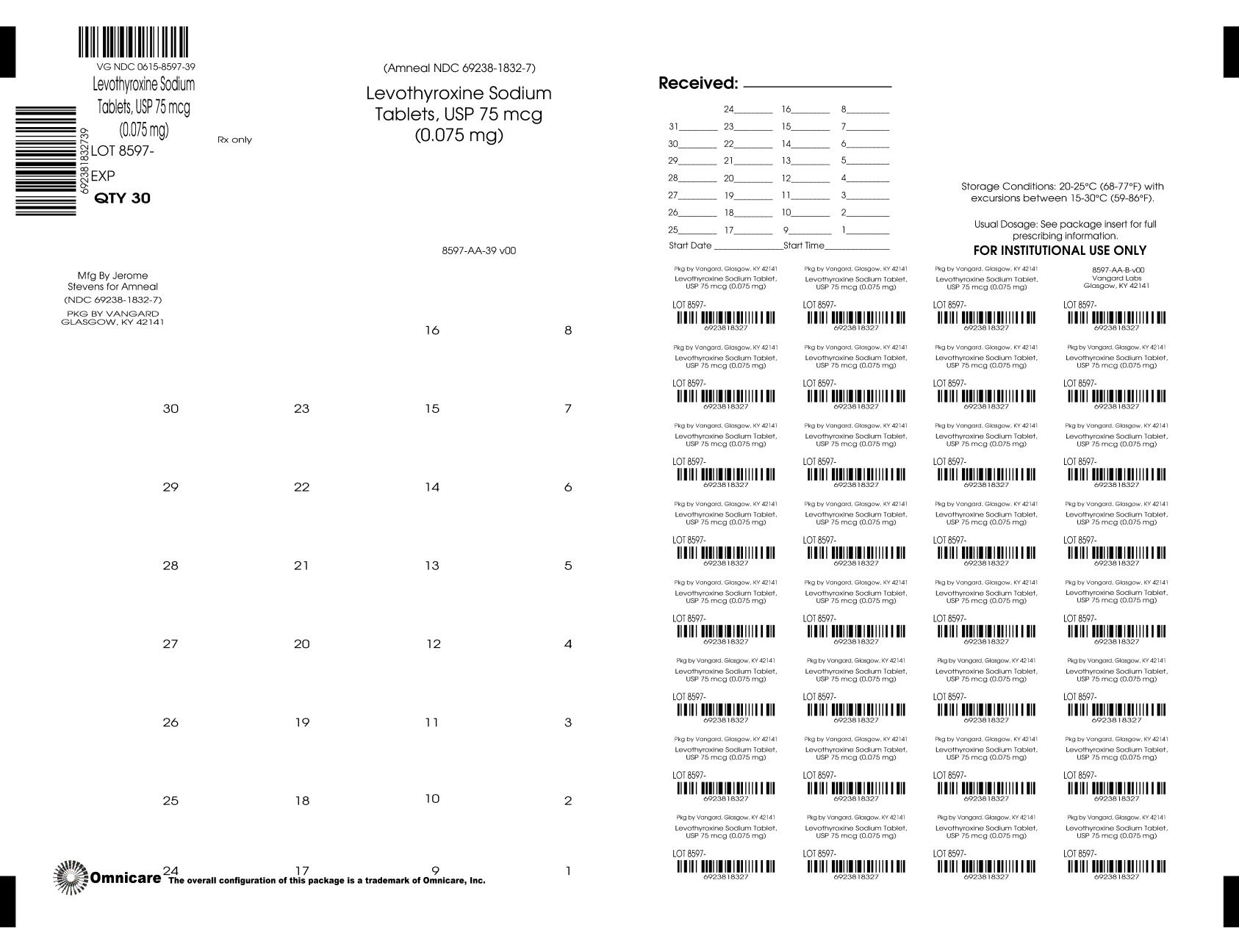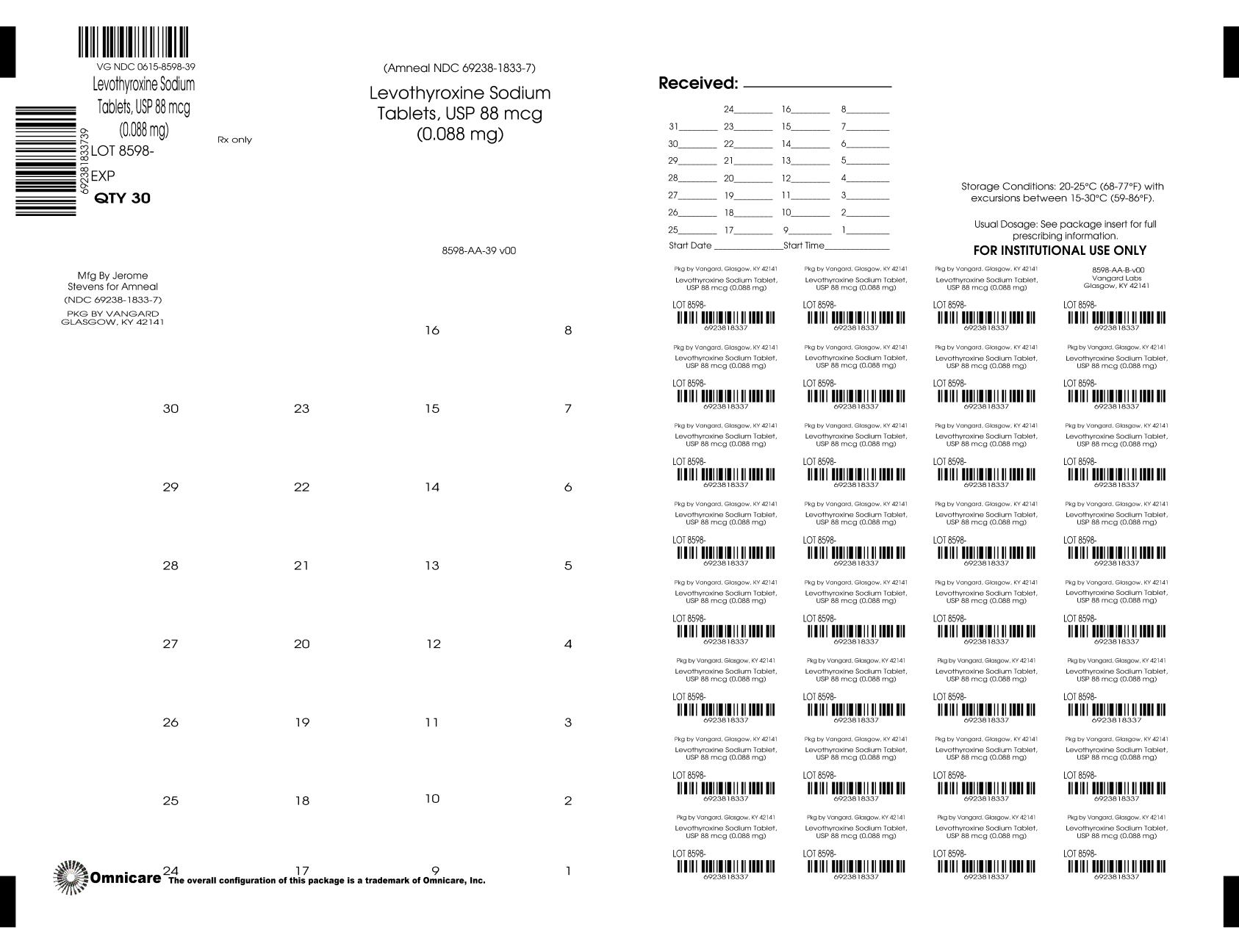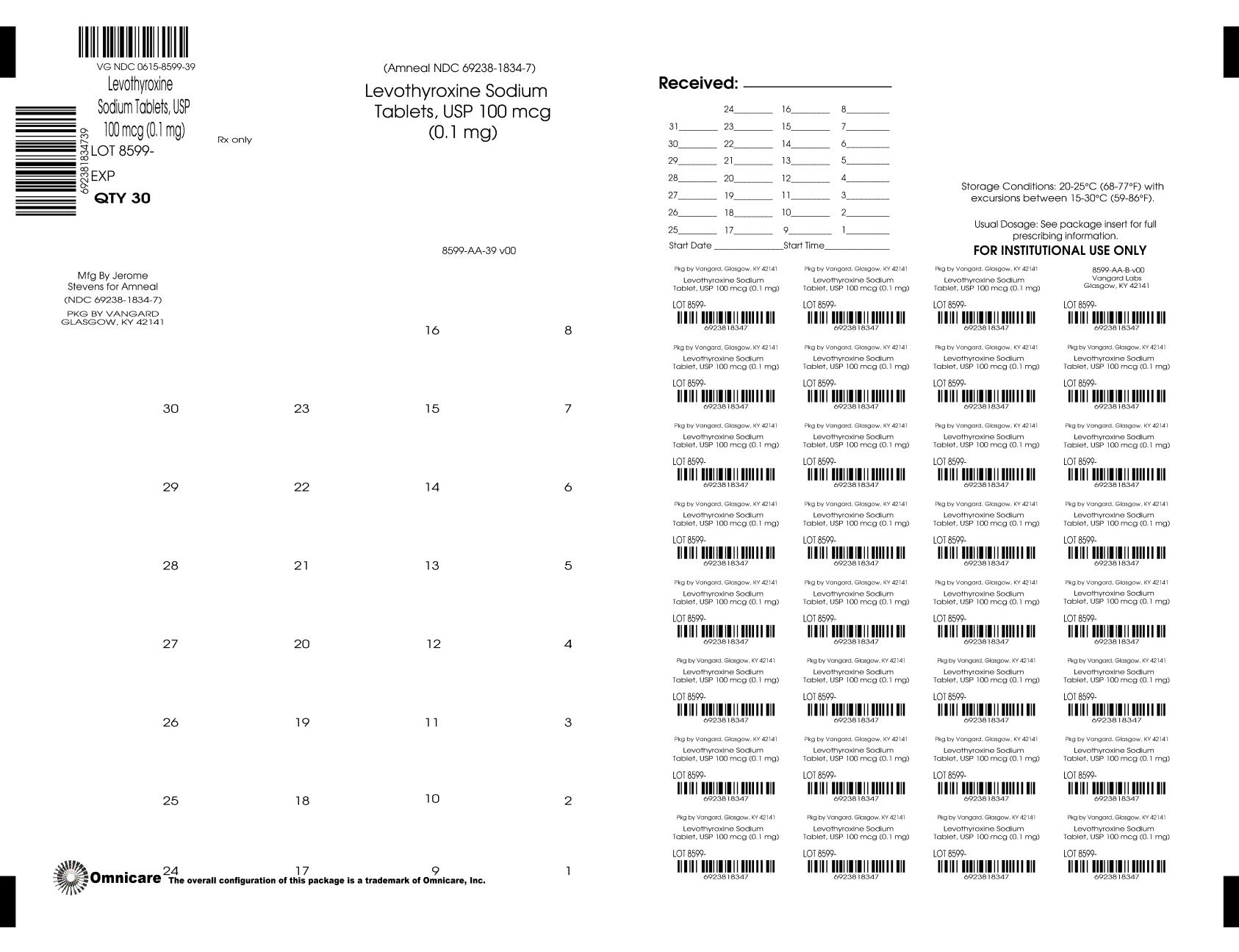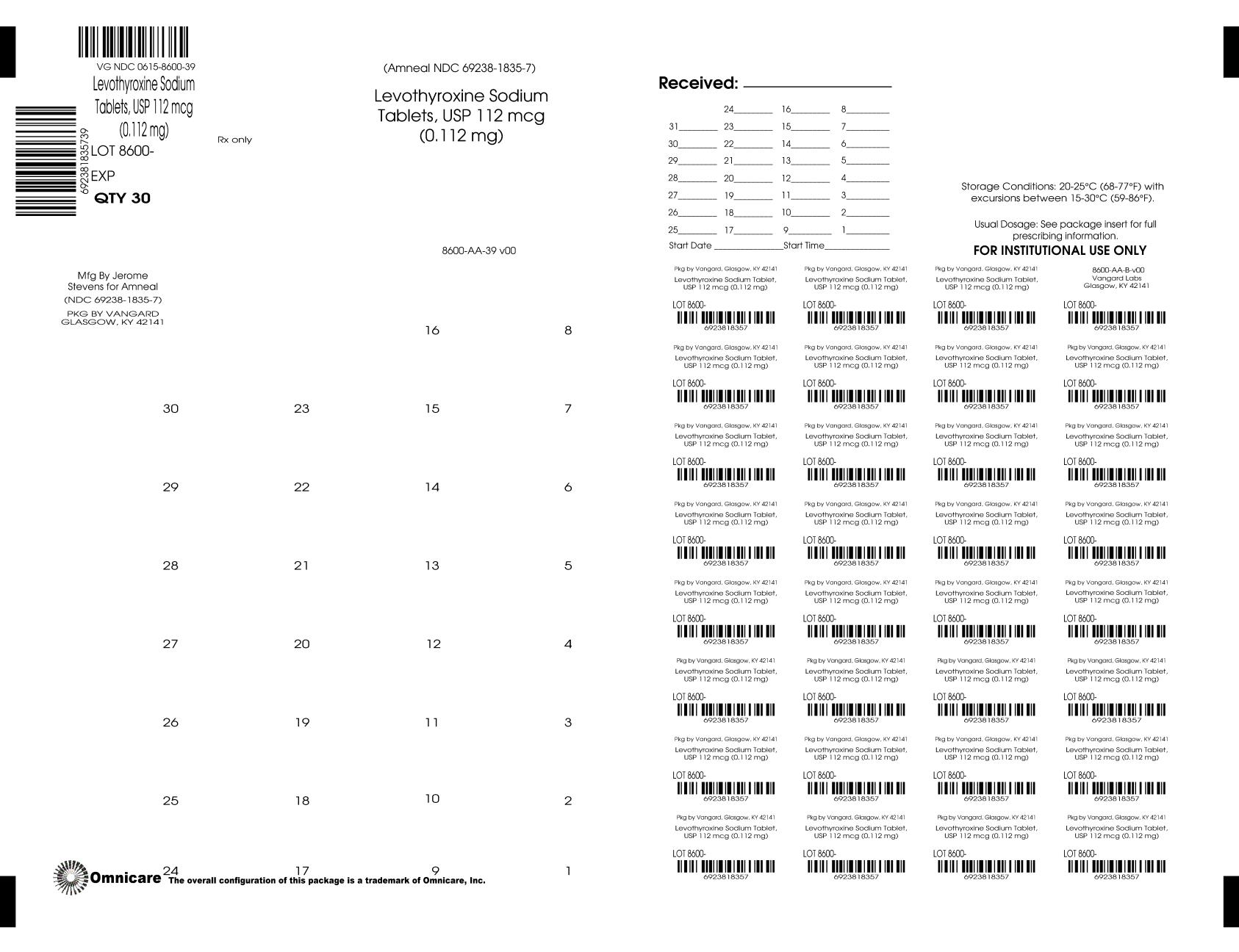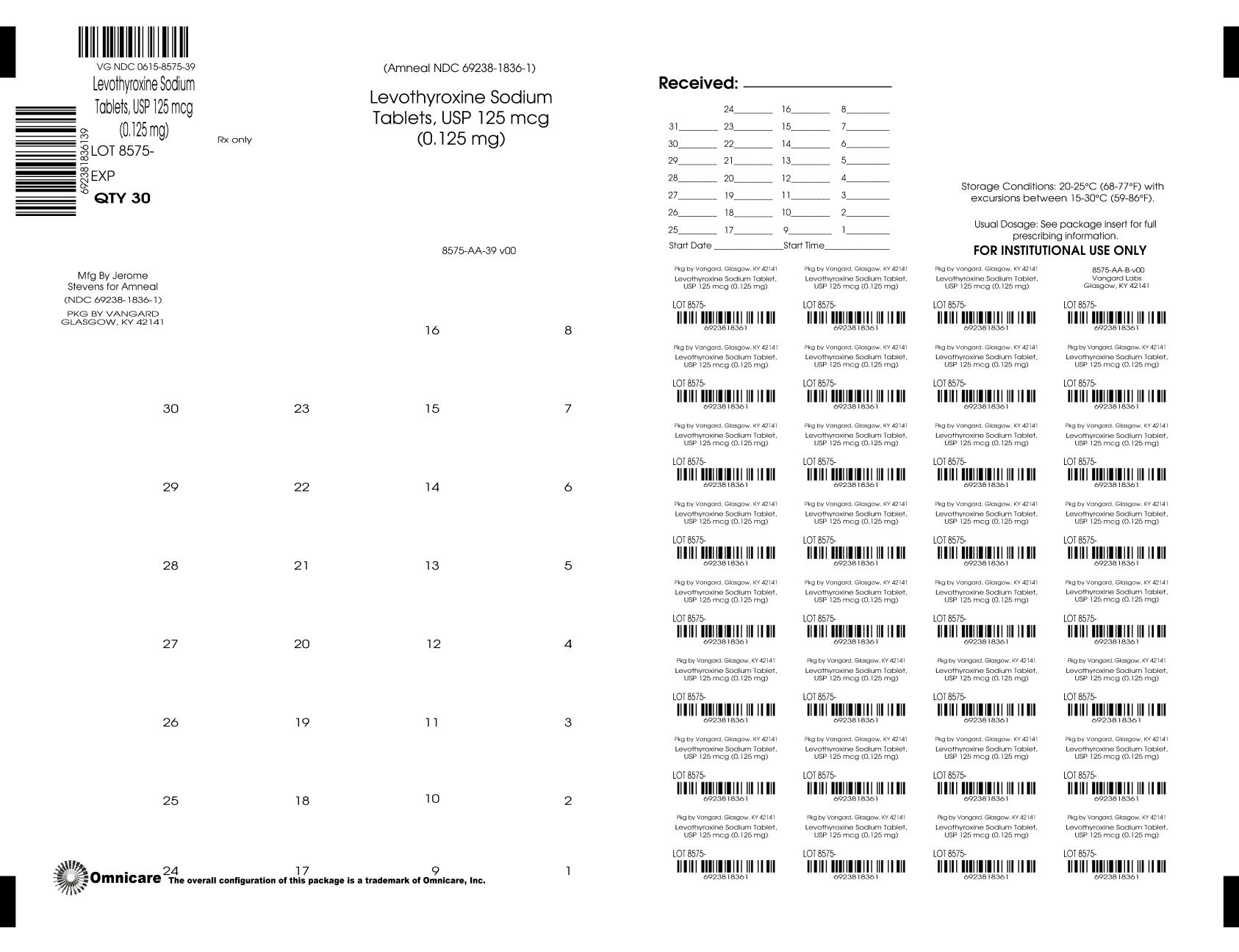 DRUG LABEL: Levothyroxine Sodium
NDC: 0615-8573 | Form: TABLET
Manufacturer: NCS HealthCare of KY, LLC dba Vangard Labs
Category: prescription | Type: HUMAN PRESCRIPTION DRUG LABEL
Date: 20260128

ACTIVE INGREDIENTS: LEVOTHYROXINE SODIUM 0.025 mg/1 1
INACTIVE INGREDIENTS: SILICON DIOXIDE; LACTOSE, UNSPECIFIED FORM; MAGNESIUM STEARATE; CELLULOSE, MICROCRYSTALLINE; STARCH, CORN; ACACIA; SODIUM STARCH GLYCOLATE TYPE A POTATO; FD&C YELLOW NO. 6; ALUMINUM OXIDE

Levothyroxine Sodium Tablets, USP

DESCRIPTION

Levothyroxine Sodium Tablets, USP contain synthetic crystalline L-3,3',5,5'-tetraiodothyronine sodium salt [levothyroxine (T4) sodium]. Synthetic T4 is identical to that produced in the human thyroid gland. Levothyroxine (T4) sodium has an empirical formula of C15H10I4N NaO4 • H2O, molecular weight of 798.86 g/mol (anhydrous), and structural formula as shown:

Inactive Ingredients

Colloidal silicon dioxide, lactose, magnesium stearate, microcrystalline cellulose, corn starch, acacia and sodium starch glycolate. The following are the coloring additives per tablet strength:

Strength (mcg) | Color Additive(s)
25 | FD&C Yellow No. 6 Aluminum Lake
50 | None
75 | FD&C Red No. 40 Aluminum Lake, FD&C Blue No. 2 Aluminum Lake
88 | D&C Yellow No. 10 Aluminum Lake, FD&C Yellow No. 6 Aluminum Lake, FD&C Blue No. 1 Aluminum Lake
100 | D&C Yellow No. 10 Aluminum Lake, FD&C Yellow No. 6 Aluminum Lake
112 | D&C Red No. 27 Aluminum Lake
125 | FD&C Yellow No. 6 Aluminum Lake, FD&C Red No. 40 Aluminum Lake, FD&C Blue No. 1 Aluminum Lake
137 | FD&C Blue No. 1 Aluminum Lake
150 | FD&C Blue No. 2 Aluminum Lake
175 | FD&C Blue No. 1 Aluminum Lake, D&C Red No. 27 Aluminum Lake
200 | FD&C Red No. 40 Aluminum Lake
300 | D&C Yellow No. 10 Aluminum Lake, FD&C Yellow No. 6 Aluminum Lake, FD&C Blue No. 1 Aluminum Lake

CLINICAL PHARMACOLOGY

Thyroid hormone synthesis and secretion is regulated by the hypothalamic-pituitary-thyroid axis. Thyrotropin-releasing hormone (TRH) released from the hypothalamus stimulates secretion of thyrotropin-stimulating hormone, TSH, from the anterior pituitary. TSH, in turn, is the physiologic stimulus for the synthesis and secretion of thyroid hormones, L-thyroxine (T4) and L-triiodothyronine (T3), by the thyroid gland. Circulating serum T3 and T4 levels exert a feedback effect on both TRH and TSH secretion. When serum T3 and T4 levels increase, TRH and TSH secretion decrease. When thyroid hormone levels decrease, TRH and TSH secretion increase.

The mechanisms by which thyroid hormones exert their physiologic actions are not completely understood, but it is thought that their principal effects are exerted through control of DNA transcription and protein synthesis. T3 and T4 diffuse into the cell nucleus and bind to thyroid receptor proteins attached to DNA. This hormone nuclear receptor complex activates gene transcription and synthesis of messenger RNA and cytoplasmic proteins.

Thyroid hormones regulate multiple metabolic processes and play an essential role in normal growth and development, and normal maturation of the central nervous system and bone. The metabolic actions of thyroid hormones include augmentation of cellular respiration and thermogenesis, as well as metabolism of proteins, carbohydrates and lipids. The protein anabolic effects of thyroid hormones are essential to normal growth and development.

The physiologic actions of thyroid hormones are produced predominately by T3, the majority of which (approximately 80%) is derived from T4 by deiodination in peripheral tissues.

Levothyroxine, at doses individualized according to patient response, is effective as replacement or supplemental therapy in hypothyroidism of any etiology, except transient hypothyroidism during the recovery phase of subacute thyroiditis.

Levothyroxine is also effective in the suppression of pituitary TSH secretion in the treatment or prevention of various types of euthyroid goiters, including thyroid nodules, Hashimoto's thyroiditis, multinodular goiter and, as adjunctive therapy in the management of thyrotropin-dependent well-differentiated thyroid cancer (see INDICATIONS AND USAGE, PRECAUTIONS, DOSAGE AND ADMINISTRATION).

PHARMACOKINETICS

Absorption - Absorption of orally administered T4 from the gastrointestinal (GI) tract ranges from 40% to 80%. The majority of the levothyroxine dose is absorbed from the jejunum and upper ileum. The relative bioavailability of Levothyroxine Sodium Tablets, USP, compared to an equal nominal dose of oral levothyroxine sodium solution, is approximately 99%. T4 absorption is increased by fasting, and decreased in malabsorption syndromes and by certain foods such as soybean infant formula. Dietary fiber decreases bioavailability of T4. Absorption may also decrease with age. In addition, many drugs and foods affect T4 absorption (see PRECAUTIONS, Drug Interactions and Drug-Food Interactions).

Distribution - Circulating thyroid hormones are greater than 99% bound to plasma proteins, including thyroxine-binding globulin (TBG), thyroxine-binding prealbumin (TBPA), and albumin (TBA), whose capacities and affinities vary for each hormone. The higher affinity of both TBG and TBPA for T4 partially explains the higher serum levels, slower metabolic clearance, and longer half-life of T4 compared to T3. Protein-bound thyroid hormones exist in reverse equilibrium with small amounts of free hormone. Only unbound hormone is metabolically active. Many drugs and physiologic conditions affect the binding of thyroid hormones to serum proteins (see PRECAUTIONS, Drug Interactions and Drug-Laboratory Test Interactions). Thyroid hormones do not readily cross the placental barrier (see PRECAUTIONS, Pregnancy).

Metabolism - T4 is slowly eliminated (see TABLE 1). The major pathway of thyroid hormone metabolism is through sequential deiodination. Approximately eighty-percent of circulating T3 is derived from peripheral T4 by monodeiodination. The liver is the major site of degradation for both T4 and T3; with T4 deiodination also occurring at a number of additional sites, including the kidney and other tissues. Approximately 80% of the daily dose of T4 is deiodinated to yield equal amounts of T3 and reverse T3 (rT3). T3 and rT3 are further deiodinated to diiodothyronine. Thyroid hormones are also metabolized via conjugation with glucuronides and sulfates and excreted directly into the bile and gut where they undergo enterohepatic recirculation.

Elimination - Thyroid hormones are primarily eliminated by the kidneys. A portion of the conjugated hormone reaches the colon unchanged and is eliminated in the feces. Approximately 20% of T4 is eliminated in the stool. Urinary excretion of T4 decreases with age.

Table 1: Pharmacokinetic Parameters of Thyroid Hormones in Euthyroid Patients
Hormone | Ratio in; Thyroglobulin | Biologic; Potency | t1/2 (days) | Protein Binding (%)^2
Levothyroxine (T4) | 10 - 20 | 1 | 6-7^1 | 99.96
Liothyronine (T3) | 1 | 4 | ≤ 2 | 99.5
^1 3 to 4 days in hyperthyroidism, 9 to 10 days in hypothyroidism;
^2 Includes TBG, TBPA, and TBA

INDICATIONS AND USAGE

Levothyroxine sodium is used for the following indications:

Hypothyroidism - As replacement or supplemental therapy in congenital or acquired hypothyroidism of any etiology, except transient hypothyroidism during the recovery phase of subacute thyroiditis. Specific indications include: primary (thyroidal), secondary (pituitary), and tertiary (hypothalamic) hypothyroidism and subclinical hypothyroidism. Primary hypothyroidism may result from functional deficiency, primary atrophy, partial or total congenital absence of the thyroid gland, or from the effects of surgery, radiation, or drugs, with or without the presence of goiter.

Pituitary TSH Suppression - In the treatment or prevention of various types of euthyroid goiters (see WARNINGS and PRECAUTIONS), including thyroid nodules (see WARNINGS and PRECAUTIONS), subacute or chronic Iymphocytic thyroiditis (Hashimoto's thyroiditis), multinodular goiter (see WARNINGS and PRECAUTIONS), and, as an adjunct to surgery and radioiodine therapy in the management of thyrotropin-dependent well-differentiated thyroid cancer.

CONTRAINDICATIONS

Levothyroxine is contraindicated in patients with untreated subclinical (suppressed serum TSH level with normal T3 and T4 levels) or overt thyrotoxicosis of any etiology and in patients with acute myocardial infarction. Levothyroxine is contraindicated in patients with uncorrected adrenal insufficiency since thyroid hormones may precipitate an acute adrenal crisis by increasing the metabolic clearance of glucocorticoids (see PRECAUTIONS). Levothyroxine Sodium Tablets, USP is contraindicated in patients with hypersensitivity to any of the inactive ingredients in Levothyroxine Sodium Tablets, USP. (See DESCRIPTION, Inactive Ingredients).

WARNINGS

BOXED WARNING

WARNING: Thyroid hormones, including Levothyroxine Sodium Tablets, USP, either alone or with other therapeutic agents, should not be used for the treatment of obesity for weight loss. In euthyroid patients, doses within the range of daily hormonal requirements are ineffective for weight reduction. Larger doses may produce serious or even life threatening manifestations of toxicity, particularly when given in association with sympathomimetic amines such as those used for their anorectic effects.

Levothyroxine sodium should not be used in the treatment of male or female infertility unless this condition is associated with hypothyroidism.

In patients with nontoxic diffuse goiter or nodular thyroid disease, particularly the elderly or those with underlying cardiovascular disease, levothyroxine sodium therapy is contraindicated if the serum TSH level is already suppressed due to the risk of precipitating overt thyrotoxicosis (see CONTRAINDICATIONS). If the serum TSH level is not suppressed, Levothyroxine Sodium Tablets, USP should be used with caution in conjunction with careful monitoring of thyroid function for evidence of hyperthyroidism and clinical monitoring for potential associated adverse cardiovascular signs and symptoms of hyperthyroidism.

PRECAUTIONS

General

Levothyroxine has a narrow therapeutic index. Regardless of the indication for use, careful dosage titration is necessary to avoid the consequences of over- or under-treatment. These consequences include, among others, effects on growth and development, cardiovascular function, bone metabolism, reproductive function, cognitive function, emotional state, gastrointestinal function, and on glucose and lipid metabolism. Many drugs interact with levothyroxine sodium necessitating adjustments in dosing to maintain therapeutic response (see Drug Interactions).

Effects on bone mineral density - In women, long-term levothyroxine sodium therapy has been associated with increased bone resorption, thereby decreasing bone mineral density, especially in post-menopausal women on greater than replacement doses or in women who are receiving suppressive doses of levothyroxine sodium. The increased bone resorption may be associated with increased serum levels and urinary excretion of calcium and phosphorous, elevations in bone alkaline phosphatase and suppressed serum parathyroid hormone levels. Therefore, it is recommended that patients receiving levothyroxine sodium be given the minimum dose necessary to achieve the desired clinical and biochemical response.

Patients with underlying cardiovascular disease - Exercise caution when administering levothyroxine to patients with cardiovascular disorders and to the elderly in whom there is an increased risk of occult cardiac disease. In these patients, levothyroxine therapy should be initiated at lower doses than those recommended in younger individuals or in patients without cardiac disease (see WARNINGS; PRECAUTIONS, Geriatric Use; and DOSAGE AND ADMINISTRATION). If cardiac symptoms develop or worsen, the levothyroxine dose should be reduced or withheld for one week and then cautiously restarted at a lower dose. Overtreatment with levothyroxine sodium may have adverse cardiovascular effects such as an increase in heart rate, cardiac wall thickness, and cardiac contractility and may precipitate angina or arrhythmias. Patients with coronary artery disease who are receiving levothyroxine therapy should be monitored closely during surgical procedures, since the possibility of precipitating cardiac arrhythmias may be greater in those treated with levothyroxine. Concomitant administration of levothyroxine and sympathomimetic agents to patients with coronary artery disease may precipitate coronary insufficiency.

Patients with nontoxic diffuse goiter or nodular thyroid disease- Exercise caution when administering levothyroxine to patients with nontoxic diffuse goiter or nodular thyroid disease in order to prevent precipitation of thyrotoxicosis (see WARNINGS). If the serum TSH is already suppressed, levothyroxine sodium should not be administered (see Contraindications).

Associated endocrine disorders

Hypothalamic/pituitary hormone deficiencies - In patients with secondary or tertiary hypothyroidism, additional hypothalamic/ pituitary hormone deficiencies should be considered, and, if diagnosed, treated (see PRECAUTIONS, Autoimmune polyglandular syndrome for adrenal insufficiency).

Autoimmune polyglandular syndrome - Occasionally, chronic autoimmune thyroiditis may occur in association with other autoimmune disorders such as adrenal insufficiency, pernicious anemia, and insulin-dependent diabetes mellitus. Patients with concomitant adrenal insufficiency should be treated with replacement glucocorticoids prior to initiation of treatment with levothyroxine sodium. Failure to do so may precipitate an acute adrenal crisis when thyroid hormone therapy is initiated, due to increased metabolic clearance of glucocorticoids by thyroid hormone. Patients with diabetes mellitus may require upward adjustments of their antidiabetic therapeutic regimens when treated with levothyroxine (see PRECAUTIONS, Drug Interactions).

Other associated medical conditions

Infants with congenital hypothyroidism appear to be at increased risk for other congenital anomalies, with cardiovascular anomalies (pulmonary stenosis, atrial septal defect, and ventricular septal defect,) being the most common association.

Information for Patients

Patients should be informed of the following information to aid in the safe and effective use of Levothyroxine Sodium Tablets, USP:

1. Notify your physician if you are allergic to any foods or medicines, are pregnant or intend to become pregnant, are breast-feeding or are taking any other medications, including prescription and over-the-counter preparations.
2. Notify your physician of any other medical conditions you may have, particularly heart disease, diabetes, clotting disorders, and adrenal or pituitary gland problems. Your dose of medications used to control these other conditions may need to be adjusted while you are taking Levothyroxine Sodium Tablets, USP. If you have diabetes, monitor your blood and/or urinary glucose levels as directed by your physician and immediately report any changes to your physician. If you are taking anticoagulants (blood thinners), your clotting status should be checked frequently.
3. Use Levothyroxine Sodium Tablets, USP only as prescribed by your physician. Do not discontinue or change the amount you take or how often you take it, unless directed to do so by your physician.
4. The levothyroxine in Levothyroxine Sodium Tablets, USP is intended to replace a hormone that is normally produced by your thyroid gland. Generally, replacement therapy is to be taken for life, except in cases of transient hypothyroidism, which is usually associated with an inflammation of the thyroid gland (thyroiditis).
5. Take Levothyroxine Sodium Tablets, USP in the morning on an empty stomach, at least one-half hour to one hour before eating any food.
6. It may take several weeks before you notice an improvement in your symptoms.
7. Notify your physician if you experience any of the following symptoms: rapid or irregular heartbeat, chest pain, shortness of breath, leg cramps, headache, nervousness, irritability, sleeplessness, tremors, change in appetite, weight gain or loss, vomiting, diarrhea, excessive sweating, heat intolerance, fever, changes in menstrual periods, hives or skin rash, or any other unusual medical event.
8. Notify your physician if you become pregnant while taking Levothyroxine Sodium Tablets, USP. It is likely that your dose of Levothyroxine Sodium Tablets, USP will need to be increased while you are pregnant.
9. Notify your physician or dentist that you are taking Levothyroxine Sodium Tablets, USP prior to any surgery.
10. Partial hair loss may occur rarely during the first few months of Levothyroxine Sodium Tablets, USP therapy, but this is usually temporary.
11. Levothyroxine Sodium Tablets, USP should not be used as a primary or adjunctive therapy in a weight control program.
12. Keep Levothyroxine Sodium Tablets, USP out of the reach of children. Store Levothyroxine Sodium Tablets, USP away from heat, moisture, and light.
13. Agents such as iron and calcium supplements and antacids can decrease the absorption of levothyroxine sodium tablets. Therefore, levothyroxine sodium tablets should not be administered within 4 hrs of these agents.

Laboratory Tests

General

The diagnosis of hypothyroidism is confirmed by measuring TSH levels using a sensitive assay (second generation assay sensitivity ≤ 0.1 mlU/L or third generation assay sensitivity ≤ 0.01 mlU/L) and measurement of free-T4.

The adequacy of therapy is determined by periodic assessment of appropriate laboratory tests and clinical evaluation. The choice of laboratory tests depends on various factors including the etiology of the underlying thyroid disease, the presence of concomitant medical conditions, including pregnancy, and the use of concomitant medications (see PRECAUTIONS, Drug Interactions and Drug-Laboratory Test Interactions). Persistent clinical and laboratory evidence of hypothyroidism despite an apparent adequate replacement dose of Levothyroxine Sodium Tablets, USP may be evidence of inadequate absorption, poor compliance, drug interactions, or decreased T4 potency of the drug product.

Adults

In adult patients with primary (thyroidal) hypothyroidism, serum TSH levels (using a sensitive assay) alone may be used to monitor therapy. The frequency of TSH monitoring during levothyroxine dose titration depends on the clinical situation but it is generally recommended at 6-8 week intervals until normalization. For patients who have recently initiated levothyroxine therapy and whose serum TSH has normalized or in patients who have had their dosage of levothyroxine changed, the serum TSH concentration should be measured after 8-12 weeks. When the optimum replacement dose has been attained, clinical (physical examination) and biochemical monitoring may be performed every 6-12 months, depending on the clinical situation, and whenever there is a change in the patient's status. It is recommended that a physical examination and a serum TSH measurement be performed at least annually in patients receiving Levothyroxine Sodium Tablets, USP. (see WARNINGS, PRECAUTIONS and DOSAGE AND ADMINISTRATION).

Pediatrics

In patients with congenital hypothyroidism, the adequacy of replacement therapy should be assessed by measuring both serum TSH (using a sensitive assay) and total- or free-T4. During the first three years of life, the serum total- or free-T4 should be maintained at all times in the upper half of the normal range. While the aim of therapy is to also normalize the serum TSH level, this is not always possible in a small percentage of patients, particularly in the first few months of therapy. TSH may not normalize due to a resetting of the pituitary-thyroid feedback threshold as a result of in utero hypothyroidism. Failure of the serum T4 to increase into the upper half of the normal range within 2 weeks of initiation of Levothyroxine Sodium Tablets, USP therapy and/or of the serum TSH to decrease below 20 mU/L within 4 weeks should alert the physician to the possibility that the child is not receiving adequate therapy. Careful inquiry should then be made regarding compliance, dose of medication administered, and method of administration prior to raising the dose of Levothyroxine Sodium Tablets, USP.

The recommended frequency of monitoring of TSH and total or free T4 in children is as follows: at 2 and 4 weeks after the initiation of treatment; every 1-2 months during the first year of life; every 2-3 months between 1 and 3 years of age; and every 3 to 12 months thereafter until growth is completed. More frequent intervals of monitoring may be necessary if poor compliance is suspected or abnormal values are obtained. It is recommended that TSH and T4 levels, and a physical examination, if indicated, be performed 2 weeks after any change in Levothyroxine Sodium Tablets, USP dosage. Routine clinical examination, including assessment of mental and physical growth and development, and bone maturation should be performed at regular intervals (see PRECAUTIONS, Pediatric Use and DOSAGE AND ADMINISTRATION).

Secondary (pituitary) and tertiary (hypothalamic) hypothyroidism

Adequacy of therapy should be assessed by measuring serum free-T4 levels, which should be maintained in the upper half of the normal range in these patients.

Drug Interactions

Many drugs affect thyroid hormone pharmacokinetics and metabolism (e.g., absorption, synthesis, secretion, catabolism, protein binding, and target tissue response) and may alter the therapeutic response to Levothyroxine Sodium Tablets, USP. In addition, thyroid hormones and thyroid status have varied effects on the pharmacokinetics and action of other drugs. A listing of drug-thyroidal axis interactions is contained in Table 2.

The list of drug-thyroidal axis interactions in Table 2 may not be comprehensive due to the introduction of new drugs that interact with the thyroidal axis or the discovery of previously unknown interactions. The prescriber should be aware of this fact and should consult appropriate reference sources (e.g., package inserts of newly approved drugs, medical literature) for additional information if a drug-drug interaction with levothyroxine is suspected.

Table 2: Drug-Thyroidal Axis Interactions
Drug or Drug Class |  |  | Effect
Drugs that may reduce TSH secretion - the reduction is not sustained; therefore, hypothyroidism does not occur
Dopamine/Dopamine Agonists Glucocorticoids Octreotide |  |  | Use of these agents may result in a transient reduction in TSH secretion when administered at the following doses: dopamine (≥ 1 mcg/kg/min); Glucocorticoids (hydrocortisone ≥ 100 mg/day or equivalent); Octreotide (> 100 mcg/day).
Drugs that alter thyroid hormone secretion
Drugs that may decrease thyroid hormone secretion, which may result in hypothyroidism
Aminoglutethimide Amiodarone Iodide (including iodine-containing Radiographic contrast agents) Lithium Methimazole Propylthioracil (PTU) Sulfonamides Tolbutamide |  |  | Long-term lithium therapy can result in goiter in up to 50% of patients, and either subclinical or overt hypothyroidism, each in up to 20% of patients. The fetus, neonate, elderly and euthyroid patients with underlying thyroid disease (e.g., Hashimoto's thyroiditis or with Grave's disease previously treated with radioiodine or surgery) are among those individuals who are particularly susceptible to iodine-induced hypothyroidism. Oral cholecystographic agents and amiodarone are slowly excreted, producing more prolonged hypothyroidism than parenterally administered iodinated contrast agents. Long-term amino-glu-tethimide therapy may minimally decrease T4 and T3 levels and increase TSH, although all values remain within normal limits in most patients.
Drugs that may increase thyroid hormone secretion, which may result in hyperthyroidism
Amiodarone Iodide (including iodine-containing Radiographic contrast agents) |  |  | Iodide and drugs that contain pharmacologic amounts of iodide may cause hyperthyroidism in euthyroid patients with Grave's disease previously treated with antithyroid drugs or in euthyroid patients with thyroid autonomy (e.g., multinodular goiter or hyper functioning thyroid adenoma). Hyperthyroidism may develop over several weeks and may persist for several months after therapy discontinuation. Amiodarone may induce hyperthyroidism by causing thyroiditis.
Drugs that may decrease T4 absorption, which may result in hypothyroidism
Antacids - Aluminum & Magnesium Hydroxides - Simethicone Bile Acid Sequestrants - Cholestyramine - Colestipol Calcium Carbonate Cation Exchange Resins - Kayexalate Ferrous Sulfate Orlistat Sucralfate |  |  | Concurrent use may reduce the efficacy of levothyroxine by binding and delaying or preventing absorption, potentially resulting in hypothyroidism. Calcium carbonate may form an insoluble chelate with levothyroxine, and ferrous sulfate likely forms a ferric-thyroxine complex. Administer levothyroxine at least 4 hours apart from these agents. Patients treated concomitantly with orlistat and levothyroxine should be monitored for changes in thyroid function.
Drugs that may alter T4 and T3 serum transport - but FT4 concentration remains normal; and, therefore, the patient remains euthyroid
Drugs that may increase serum TBG concentration |  |  | Drugs that may decrease serum TBG concentration
Clofibrate Estrogen-containing oral contraceptives Estrogens (oral) Heroin / Methadone 5-Fluorouracil Mitotane Tamoxifen |  |  | Androgens / Anabolic Steroids Asparaginase Glucocorticoids Slow-Release Nicotinic Acid
Drugs that may cause protein-binding site displacement
Furosemide (> 80 mg IV) Heparin Hydantoins Non Steroidal Anti-lnflammatory Drugs - Fenamates - Phenylbutazone Salicylates (> 2 g/day) |  |  | Administration of these agents with levothyroxine results in an initial transient increase in FT4. Continued administration results in a decrease in serum T4 and normal FT4 and TSH concentrations and, therefore, patients are clinically euthyroid. Salicylates inhibit binding of T4 and T3 to TBG and transthyretin. An initial increase in serum FT4, is followed by return of FT4 to normal levels with sustained therapeutic serum salicylate concentrations, although total-T4 levels may decrease by as much as 30%.
Drugs that may alter T4 and T3 metabolism
Drugs that may increase hepatic metabolism, which may result in hypothyroidism
Carbamazepine Hydantoins Phenobarbital Rifampin |  |  | Stimulation of hepatic microsomal drug-metabolizing enzyme activity may cause increased hepatic degradation of levothyroxine, resulting in increased Ievothyroxine requirements. Phenytoin and carbamazepine reduce serum protein binding of levothyroxine, and total- and free-T4 may be reduced by 20% to 40%, but most patients have normal serum TSH levels and are clinically euthyroid.
Drugs that may decrease T4 5' - deiodinase activity
Amiodarone Beta-adrenergic antagonists - (e.g., Propranolol > 160 mg/day) Glucocorticoids -(e.g., Dexamethasone ≥ 4 mg/day) Propylthiouracil (PTU) |  |  | Administration of these enzyme inhibitors decrease the peripheral conversion of T4 to T3, leading to decreased T3 levels. However, serum T4 levels are usually normal but may occasionally be slightly increased. In patients treated with large doses of propranolol (> 160 mg/day), T3 and T4 levels change slightly, TSH levels remain normal, and patients are clinically euthyroid. It should be noted that actions of particular beta-adrenergic antagonists may be impaired when the hypothyroid patient is converted to the euthyroid state. Short-term administration of large doses of glucocorticoids may decrease serum T3 concentrations by 30% with minimal change in serum T4 levels. However, long-term glucocorticoid therapy may result in slightly decreased T3 and T4 levels due to decreased TBG production (see above).
Miscellaneous
Anticoagulants (oral) - Coumarin Derivatives - Indandione Derivatives |  |  | Thyroid hormones appear to increase the catabolism of vitamin K-dependent clotting factors, thereby increasing the anticoagulant activity of oral anticoagulants. Concomitant use of these agents impairs the compensatory increases in clotting factor synthesis. Prothrombin time should be carefully monitored in patients taking levothyroxine and oral anticoagulants and the dose of anticoagulant therapy adjusted accordingly.
Antidepressants - Tricyclics (e.g., Amitriptyline) - Tetracyclics (e.g., Maprotiline) - Selective Serotonin Reuptake Inhibitors (SSRIs; e.g., Sertraline) |  |  | Concurrent use of tri/tetracyclic antidepressants and levothyroxine may increase the therapeutic and toxic effects of both drugs, possibly due to increased receptor sensitivity to catecholamines.Toxic effects may include increased risk of cardiac arrhythmias and CNS stimulation; onset of action of tricyclics may be accelerated. Administration of sertraline in patients stabilized on levothyroxine may result in increased levothyroxine requirements.
Antidiabetic Agents - Biguanides - Meglitinides - Sulfonylureas - Thiazolidediones - Insulin |  |  | Addition of levothyroxine to antidiabetic or insulin therapy may result in increased antidiabetic agent or insulin requirements. Careful monitoring of diabetic control is recommended, especially when thyroid therapy is started, changed, or discontinued.
Cardiac Glycosides |  |  | Serum digitalis glycoside levels may be reduced in hyperthyroidism or when the hypothyroid patient is converted to the euthyroid state. Therapeutic effect of digitalis glycosides may be reduced.
Cytokines - Interferon-α - Interleukin-2 |  |  | Therapy with interferon-α has been associated with the development of antithyroid microsomal antibodies in 20% of patients and some have transient hypothyroidism, hyperthyroidism, or both. Patients who have antithyroid antibodies before treatment are at higher risk for thyroid dysfunction during treatment. Interleukin-2 has been associated with transient painless thyroiditis in 20% of patients. Interferon-β and -γ have not been reported to cause thyroid dysfunction.
Growth Hormones - Somatrem - Somatropin |  |  | Excessive use of thyroid hormones with growth hormones may accelerate epiphyseal closure. However, untreated hypothyroidism may interfere with growth response to growth hormone.
Ketamine |  |  | Concurrent use may produce marked hypertension and tachycardia; cautious administration to patients receiving thyroid hormone therapy is recommended.
Methylxanthine Bronchodilators - (e.g., Theophylline) |  |  | Decreased theophylline clearance may occur in hypothyroid patients; clearance returns to normal when the euthyroid state is achieved.
Radiographic Agents |  |  | Thyroid hormones may reduce the uptake of ^123I, ^131I, and 99mTc.
Sympathomimetics |  |  | Concurrent use may increase the effects of sympathomimetics or thyroid hormone. Thyroid hormones may increase the risk of coronary insufficiency when sympathomimetic agents are administered to patients with coronary artery disease.
Chloral Hydrate Diazepam Ethionamide Lovastatin Metoclopramide 6-Mercaptopurine Nitroprusside Para-aminosalicylate sodium Perphenazine Resorcinol (excessive topical use) Thiazide Diuretics |  |  | These agents have been associated with thyroid hormone and/or TSH level alterations by various mechanisms.

Oral anticoagulants - Levothyroxine increases the response to oral anticoagulant therapy. Therefore, a decrease in the dose of anticoagulant may be warranted with correction of the hypothyroid state or when the Levothyroxine Sodium Tablets, USP dose is increased. Prothrombin time should be closely monitored to permit appropriate and timely dosage adjustments (see Table 2).

Digitalis glycosides - The therapeutic effects of digitalis glycosides may be reduced by levothyroxine. Serum digitalis glycoside levels may be decreased when a hypothyroid patient becomes euthyroid, necessitating an increase in the dose of digitalis glycosides (see Table 2).

Drug-Food Interactions

Consumption of certain foods may affect levothyroxine absorption thereby necessitating adjustments in dosing. Soybean flour (infant formula), cotton seed meal, walnuts, and dietary fiber may bind and decrease the absorption of levothyroxine sodium from the GI tract.

Drug-Laboratory Test Interactions

Changes in TBG concentration must be considered when interpreting T4 and T3 values, which necessitates measurement and evaluation of unbound (free) hormone and/or determination of the free T4 index (FT4I). Pregnancy, infectious hepatitis, estrogens, estrogen-containing oral contraceptives, and acute intermittent porphyria increase TBG concentrations. Decreases in TBG concentrations are observed in nephrosis, severe hypoproteinemia, severe liver disease, acromegaly, and after androgen or corticosteroid therapy (see also Table 2). Familial hyper- or hypo-thyroxine binding globulinemias have been described, with the incidence of TBG deficiency approximating 1 in 9000.

Carcinogenesis, Mutagenesis, and Impairment of Fertility

Animal studies have not been performed to evaluate the carcinogenic potential, mutagenic potential or effects on fertility of levothyroxine. The synthetic T4 in Levothyroxine Sodium Tablets, USP is identical to that produced naturally by the human thyroid gland. Although there has been a reported association between prolonged thyroid hormone therapy and breast cancer, this has not been confirmed. Patients receiving Levothyroxine Sodium Tablets, USP for appropriate clinical indications should be titrated to the lowest effective replacement dose.

Pregnancy - Category A

Studies in women taking levothyroxine sodium during pregnancy have not shown an increased risk of congenital abnormalities. Therefore, the possibility of fetal harm appears remote. Levothyroxine Sodium Tablets, USP should not be discontinued during pregnancy and hypothyroidism diagnosed during pregnancy should be promptly treated.

Hypothyroidism during pregnancy is associated with a higher rate of complications, including spontaneous abortion, pre-eclampsia, stillbirth and premature delivery. Maternal hypothyroidism may have an adverse effect on fetal and childhood growth and development. During pregnancy, serum T4 levels may decrease and serum TSH levels increase to values outside the normal range. Since elevations in serum TSH may occur as early as 4 weeks gestation, pregnant women taking Levothyroxine Sodium Tablets, USP should have their TSH measured during each trimester. An elevated serum TSH level should be corrected by an increase in the dose of Levothyroxine Sodium Tablets, USP. Since postpartum TSH levels are similar to preconception values, the Levothyroxine Sodium Tablets, USP dosage should return to the pre-pregnancy dose immediately after delivery. A serum TSH level should be obtained 6-8 weeks postpartum.

Thyroid hormones cross the placental barrier to some extent as evidenced by levels in cord blood of athyroceotic fetuses being approximately one third maternal levels. Transfer of thyroid hormone from the mother to the fetus, however, may not be adequate to prevent in utero, hypothyroidism.

Nursing Mothers

Although thyroid hormones are excreted only minimally in human milk, caution should be exercised when Levothyroxine Sodium Tablets, USP is administered to a nursing woman. However, adequate replacement doses of levothyroxine are generally needed to maintain normal lactation.

Pediatric Use

General

The goal of treatment in pediatric patients with hypothyroidism is to achieve and maintain normal intellectual and physical growth and development.

The initial dose of levothyroxine varies with age and body weight (see DOSAGE AND ADMINISTRATION, Table 3). Dosing adjustments are based on an assessment of the individual patient's clinical and laboratory parameters (see PRECAUTIONS, Laboratory Tests).

In children in whom a diagnosis of permanent hypothyroidism has not been established, it is recommended that levothyroxine administration be discontinued for a 30-day trial period, but only after the child is at least 3 years of age. Serum T4 and TSH levels should then be obtained. If the T4 is low and the TSH high, the diagnosis of permanent hypothyroidism is established, and levothyroxine therapy should be reinstituted. If the T4 and TSH levels are normal, euthyroidism may be assumed and, therefore, the hypothyroidism can be considered to have been transient. In this instance, however, the physician should carefully monitor the child and repeat the thyroid function tests if any signs or symptoms of hypothyroidism develop. In this setting, the clinician should have a high index of suspicion of relapse. If the results of the levothyroxine withdrawal test are inconclusive, careful follow-up and subsequent testing will be necessary.

Since some more severely affected children may become clinically hypothyroid when treatment is discontinued for 30 days, an alternate approach is to reduce the replacement dose of levothyroxine by half during the 30-day trial period. If, after 30 days, the serum TSH is elevated above 20 mU/L, the diagnosis of permanent hypothyroidism is confirmed, and full replacement therapy should be resumed. However, if the serum TSH has not risen to greater than 20 mU/L, levothyroxine treatment should be discontinued for another 30-day trial period followed by repeat serum T4 and TSH.

The presence of concomitant medical conditions should be considered in certain clinical circumstances and, if present, appropriately treated (see PRECAUTIONS).

Congenital Hypothyroidism (see PRECAUTIONS, Laboratory Tests and DOSAGE AND ADMINISTRATION)

Rapid restoration of normal serum T4 concentrations is essential for preventing the adverse effects of congenital hypothyroidism on intellectual development as well as on overall physical growth and maturation. Therefore, Levothyroxine Sodium Tablets, USP therapy should be initiated immediately upon diagnosis and is generally continued for life.

During the first 2 weeks of Levothyroxine Sodium Tablets, USP therapy, infants should be closely monitored for cardiac overload, arrhythmias, and aspiration from avid suckling.

The patient should be monitored closely to avoid undertreatment or overtreatment. Undertreatment may have deleterious effects on intellectual development and linear growth. Overtreatment has been associated with craniosynostosis in infants, and may adversely affect the tempo of brain maturation and accelerate the bone age with resultant premature closure of the epiphyses and compromised adult stature.

Acquired Hypothyroidism in Pediatric Patients

The patient should be monitored closely to avoid undertreatment and overtreatment. Undertreatment may result in poor school performance due to impaired concentration and slowed mentation and in reduced adult height. Overtreatment may accelerate the bone age and result in premature epiphyseal closure and compromised adult stature.

Treated children may manifest a period of catch-up growth, which may be adequate in some cases to normalize adult height. In children with severe or prolonged hypothyroidism, catch-up growth may not be adequate to normalize adult height.

Geriatric Use

Because of the increased prevalence of cardiovascular disease among the elderly, levothyroxine therapy should not be initiated at the full replacement dose (see WARNINGS, PRECAUTIONS and DOSAGE AND ADMINISTRATION).

ADVERSE REACTIONS

Adverse reactions associated with levothyroxine therapy are primarily those of hyperthyroidism due to therapeutic overdosage (see PRECAUTIONS and OVERDOSAGE). They include the following:

General: fatigue, increased appetite, weight loss, heat intolerance, fever, excessive sweating;

Central nervous system: headache, hyperactivity, nervousness, anxiety, irritability, emotional lability, insomnia;

Musculoskeletal: tremors, muscle weakness;

Cardiovascular: palpitations, tachycardia, arrhythmias, increased pulse and blood pressure, heart failure, angina, myocardial infarction, cardiac arrest;

Respiratory: dyspnea;

Gastrointestinal: diarrhea, vomiting, abdominal cramps and elevation in liver function tests;

Dermatologic: hair loss; flushing;

Endocrine: decreased bone mineral density;

Reproductive: menstrual irregularities, impaired fertility.

Pseudotumor cerebri and slipped capital femoral epiphysis have been reported in children receiving levothyroxine therapy. Overtreatment may result in craniosynostosis in infants and premature closure of the epiphyses in children with resultant compromised height.

Seizures have been reported rarely with the institution of levothyroxine therapy.

Inadequate levothyroxine dosage will produce or fail to ameliorate the signs and symptoms of hypothyroidism.

Hypersensitivity reactions to inactive ingredients have occurred in patients treated with thyroid hormone products. These include urticaria, pruritus, skin rash, flushing, angioedema, various Gl symptoms (abdominal pain, nausea, vomiting and diarrhea), fever, arthralgia, serum sickness and wheezing. Hypersensitivity to levothyroxine itself is not known to occur.

OVERDOSAGE

The signs and symptoms of overdosage are those of hyperthyroidism (see PRECAUTIONS and ADVERSE REACTIONS). In addition, confusion and disorientation may occur. Cerebral embolism, shock, coma, and death have been reported. Seizures have occurred in a child ingesting 18 mg of levothyroxine. Symptoms may not necessarily be evident or may not appear until several days after ingestion of levothyroxine sodium.

Treatment of Overdosage

Levothyroxine sodium should be reduced in dose or temporarily discontinued if signs or symptoms of overdosage occur.

Acute Massive Overdosage - This may be a life-threatening emergency, therefore, symptomatic and supportive therapy should be instituted immediately. If not contraindicated (e.g., by seizures, coma, or loss of the gag reflex), the stomach should be emptied by emesis or gastric lavage to decrease gastrointestinal absorption. Activated charcoal or cholestyramine may also be used to decrease absorption. Central and peripheral increased sympathetic activity may be treated by administering β-receptor antagonists, e.g., propranolol, provided there are no medical contraindications to their use. Provide respiratory support as needed; control congestive heart failure and arrhythmia; control fever, hypoglycemia, and fluid loss as necessary. Large doses of antithyroid drugs (e.g., methimazole or propylthiouracil) followed in one to two hours by large doses of iodine may be given to inhibit synthesis and release of thyroid hormones. Glucocorticoids may be given to inhibit the conversion of T4 to T3. Plasmapheresis, charcoal hemoperfusion and exchange transfusion have been reserved for cases in which continued clinical deterioration occurs despite conventional therapy. Because T4 is highly protein bound, very little drug will be removed by dialysis.

DOSAGE AND ADMINISTRATION

General Principles:

The goal of replacement therapy is to achieve and maintain a clinical and biochemical euthyroid state. The goal of suppressive therapy is to inhibit growth and/or function of abnormal thyroid tissue. The dose of Levothyroxine Sodium Tablets, USP that is adequate to achieve these goals depends on a variety of factors including the patient's age, body weight, cardiovascular status, concomitant medical conditions, including pregnancy, concomitant medications, and the specific nature of the condition being treated (see WARNINGS and PRECAUTIONS). Hence, the following recommendations serve only as dosing guidelines. Dosing must be individualized and adjustments made based on periodic assessment of the patient's clinical response and laboratory parameters (see PRECAUTIONS, Laboratory Tests).

Levothyroxine Sodium Tablets, USP should be taken in the morning on an empty stomach, at least one-half hour to one hour before any food is eaten. Levothyroxine Sodium Tablets, USP should be taken at least 4 hours apart from drugs that are known to interfere with its absorption (see PRECAUTIONS, Drug Interactions).

Due to the long half-life of levothyroxine, the peak therapeutic effect at a given dose of levothyroxine sodium may not be attained for 4-6 weeks.

Caution should be exercised when administering Levothyroxine Sodium Tablets, USP to patients with underlying cardiovascular disease, to the elderly, and to those with concomitant adrenal insufficiency (see PRECAUTIONS).

Specific Patient Populations:

Hypothyroidism in Adults and in Children in Whom Growth and Puberty are Complete (see WARNINGS and PRECAUTIONS, Laboratory Tests).

Therapy may begin at full replacement doses in otherwise healthy individuals less than 50 years old and in those older than 50 years who have been recently treated for hyperthyroidism or who have been hypothyroid for only a short time (such as a few months). The average full replacement dose of levothyroxine sodium is approximately 1.7 mcg/kg/day (e.g., 100-125 mcg/day for a 70 kg adult). Older patients may require less than 1 mcg/kg/day. Levothyroxine sodium doses greater than 200 mcg/day are seldom required. An inadequate response to daily doses ≥ 300 mcg/day is rare and may indicate poor compliance, malabsorption, and/or drug interactions.

For most patients older than 50 years or for patients under 50 years of age with underlying cardiac disease, an initial starting dose of 25-50 mcg/day of levothyroxine sodium is recommended, with gradual increments in dose at 6-8 week intervals, as needed. The recommended starting dose of levothyroxine sodium in elderly patients with cardiac disease is 12.5-25 mcg/day, with gradual dose increments at 4-6 week intervals. The levothyroxine sodium dose is generally adjusted in 12.5-25 mcg increments until the patient with primary hypothyroidism is clinically euthyroid and the serum TSH has normalized.

In patients with severe hypothyroidism, the recommended initial levothyroxine sodium dose is 12.5-25 mcg/day with increases of 25 mcg/day every 2-4 weeks, accompanied by clinical and laboratory assessment, until the TSH level is normalized.

In patients with secondary (pituitary) or tertiary (hypothalamic) hypothyroidism, the levothyroxine sodium dose should be titrated until the patient is clinically euthyroid and the serum free-T4 level is restored to the upper half of the normal range.

Pediatric Dosage - Congenital or Acquired Hypothyroidism (see PRECAUTIONS, Laboratory Tests)

General Principles

In general, levothyroxine therapy should be instituted at full replacement doses as soon as possible. Delays in diagnosis and institution of therapy may have deleterious effects on the child's intellectual and physical growth and development.

Undertreatment and overtreatment should be avoided (see PRECAUTIONS, Pediatric Use).

Levothyroxine Sodium Tablets, USP may be administered to infants and children who cannot swallow intact tablets by crushing the tablet and suspending the freshly crushed tablet in a small amount (5-10 mL or 1-2 teaspoons) of water. This suspension can be administered by spoon or dropper. DO NOT STORE THE SUSPENSION. Foods that decrease absorption of levothyroxine, such as soybean infant formula, should not be used for administering levothyroxine sodium tablets. (see PRECAUTIONS, Drug-Food Interactions).

Newborns

The recommended starting dose of levothyroxine sodium in newborn infants is 10-15 mcg/kg/day. A lower starting dose (e.g., 25 mcg/day) should be considered in infants at risk for cardiac failure, and the dose should be increased in 4-6 weeks as needed based on clinical and laboratory response to treatment. In infants with very low (< 5 mcg/dL) or undetectable serum T4 concentrations, the recommended initial starting dose is 50 mcg/day of levothyroxine sodium.

Infants and Children

Levothyroxine therapy is usually initiated at full replacement doses, with the recommended dose per body weight decreasing with age (see TABLE 3). However, in children with chronic or severe hypothyroidism, an initial dose of 25 mcg/day of levothyroxine sodium is recommended with increments of 25 mcg every 2-4 weeks until the desired effect is achieved.

Hyperactivity in an older child can be minimized if the starting dose is one-fourth of the recommended full replacement dose, and the dose is then increased on a weekly basis by an amount equal to one-fourth the full-recommended replacement dose until the full recommended replacement dose is reached.

Table 3: Levothyroxine Sodium Dosing Guidelines for Pediatric Hypothyroidism
AGE | Daily Dose Per Kg Body Weighta
0-3 months | 10-15 mcg/kg/day
3-6 months | 8-10 mcg/kg/day
6-12 months | 6-8 mcg/kg/day
1-5 years | 5-6 mcg/kg/day
6-12 years | 4-5 mcg/kg/day
>12 years but growth and puberty incomplete | 2-3 mcg/kg/day
Growth and puberty complete | 1.7 mcg/kg/day
a. The dose should be adjusted based on clinical response and laboratory parameters (see PRECAUTlONS, Laboratory Tests and Pediatric Use).

Pregnancy- Pregnancy may increase levothyroxine requirements (see PREGNANCY).

Subclinical Hypothyroidism- If this condition is treated, a lower levothyroxine sodium dose (e.g., 1 mcg/kg/day) than that used for full replacement may be adequate to normalize the serum TSH level. Patients who are not treated should be monitored yearly for changes in clinical status and thyroid laboratory parameters.

TSH Suppression in Well-differentiated Thyroid Cancer and Thyroid Nodules- The target level for TSH suppression in these conditions has not been established with controlled studies. In addition, the efficacy of TSH suppression for benign nodular disease is controversial. Therefore, the dose of Levothyroxine Sodium Tablets, USP used for TSH suppression should be individualized based on the specific disease and the patient being treated.

In the treatment of well differentiated (papillary and follicular) thyroid cancer, levothyroxine is used as an adjunct to surgery and radioiodine therapy. Generally, TSH is suppressed to <0.1 mU/L, and this usually requires a levothyroxine sodium dose of greater than 2 mcg/kg/day. However, in patients with high-risk tumors, the target level for TSH suppression may be <0.01 mU/L.

In the treatment of benign nodules and nontoxic multinodular goiter, TSH is generally suppressed to a higher target (e.g., 0.1-0.5 mU/L for nodules and 0.5-1.0 mU/L for multinodular goiter) than that used for the treatment of thyroid cancer. Levothyroxine sodium is contraindicated if the serum TSH is already suppressed due to the risk of precipitating overt thyrotoxicosis (see CONTRAINDICATIONS, WARNINGS and PRECAUTIONS).

Myxedema Coma - Myxedema coma is a life-threatening emergency characterized by poor circulation and hypometabolism, and may result in unpredictable absorption of levothyroxine sodium from the gastrointestinal tract. Therefore, oral thyroid hormone drug products are not recommended to treat this condition. Thyroid hormone products formulated for intravenous administration should be administered.

HOW SUPPLIED

Levothyroxine Sodium Tablets, USP are round, color coded, partial bisected tablets debossed with JSP and ID Number:

Strength (mcg) | Color | NDC# for blistercards of 30 | NDC# for blistercards of 15 | NDC# for blistercards of 14
25 | Peach | NDC 0615-8573-39 | N/A | NDC 0615-8573-14
50 | White | NDC 0615-8574-39 | NDC 0615-8574-05 | NDC 0615-8574-14
75 | Purple | NDC 0615-8597-39 | NDC 0615-8597-05 | NDC 0615-8597-14
88 | Olive | NDC 0615-8598-39 | N/A | NDC 0615-8598-14
100 | Yellow | NDC 0615-8599-39 | N/A | NDC 0615-8599-14
112 | Rose | NDC 0615-8600-39 | N/A | NDC 0615-8600-14
125 | Tan | NDC 0615-8575-39 | N/A | NDC 0615-8575-14
137 | Blue | N/A | N/A | N/A
150 | Lt. Blue | N/A | N/A | N/A
175 | Lilac | N/A | N/A | N/A
200 | Pink | N/A | N/A | N/A
300 | Green | N/A | N/A | N/A

STORAGE CONDITIONS

20°C to 25°C (68°F to 77°F) with excursions between 15°C to 30°C (59°F to 86°F)

Rx only

Manufactured for:

Amneal Pharmaceuticals LLC

Bridgewater, NJ 08807

Manufactured by:
Jerome Stevens Pharmaceuticals, Inc.
Bohemia, NY 11716

Rev. 10/18

MG #18326